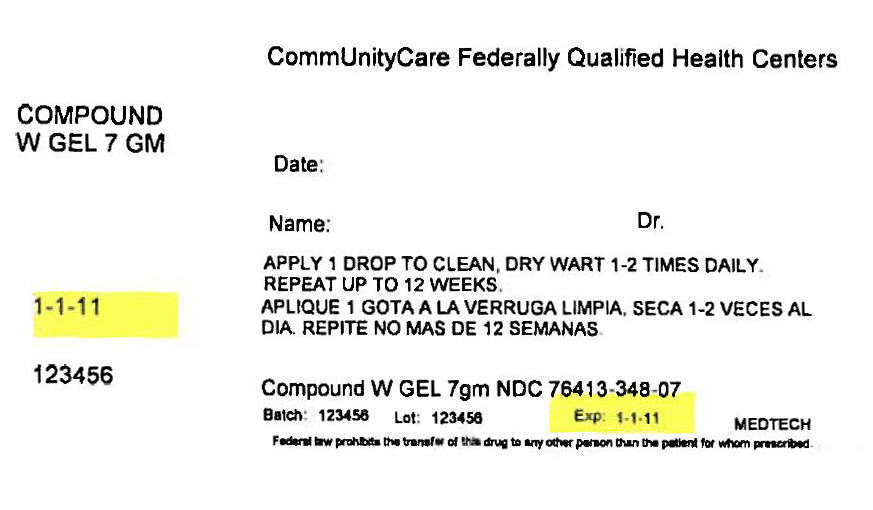 DRUG LABEL: Compound W
NDC: 76413-348 | Form: GEL
Manufacturer: Central Texas Community Health Centers
Category: otc | Type: HUMAN OTC DRUG LABEL
Date: 20171204

ACTIVE INGREDIENTS: SALICYLIC ACID 0.17 g/7 g
INACTIVE INGREDIENTS: ALCOHOL; CAMPHOR (NATURAL); CASTOR OIL; ETHYL ACETATE; HYDROXYPROPYL CELLULOSE (1200000 MW); HYPOPHOSPHOROUS ACID; ISOPROPYL ALCOHOL; PYROXYLIN; POLYSORBATE 80

Compound W Gel

Compound W®
Salicylic Acid Wart Remover

MAXIMUM STRENGTH
FAST ACTING GEL

NET WT 0.25 OZ (7 g)

Drug Facts

Active ingredient

Salicylic acid 17% w/w

Purpose

Wart remover

Use

- for the removal of common and plantar warts.
- the common wart is easily recognized by the rough "cauliflower-like" appearance on the surface.
- the plantar wart is recognized by its location only on the bottom of the foot, its tenderness, and the interruption of the footprint pattern.

Warnings

For external use only.

Flammable. Keep away from fire and flame.

Do not use

- on irritated skin or on any area that is infected or reddened.
- on moles, birthmarks, warts with hair growing from them, genital warts or warts on the face or mucous membranes.
- if you have diabetes or poor blood circulation.

When using this product

- avoid contact with eyes. If product gets into the eye, flush with water for 15 minutes.
- avoid inhaling vapors
- cap tightly and store at room temperature away from heat

Stop use and ask a doctor if

discomfort persists.

Keep out of reach of children.

If swallowed, get medical help or contact a Poison Control Center (1-800-222-1222) right away.

Directions

- wash affected area
- may soak wart in warm water for 5 minutes
- dry area thoroughly
- by squeezing tube gently, apply one drop at a time to sufficiently cover each wart
- let dry
- repeat this procedure once or twice daily as needed (until wart is removed) for up to 12 weeks

Inactive ingredients

alcohol, camphor, castor oil, ethyl acetate, hydroxypropyl cellulose, hypophosphorous acid, isopropanol, nitrocellulose, polysorbate 80

Questions?

1-800-443-4908 CompoundW.com

©2016 Distributed by Medtech Products Inc.
Tarrytown, NY 10591
A Prestige Brands Company
Made in Brazil

PRINCIPAL DISPLAY PANEL - 7 gm Tube Box Label

CommUnityCare Federally Qualified Health Centers

COMPOUND
W GEL 7 GM

Date:

Name:
Dr.

APPLY 1 DROP TO CLEAN, DRY WART 1-2 TIMES DAILY.
REPEAT UP TO 12 WEEKS.

1-1-11

123456

Compound W GEL 7gm NDC 76413-348-07

Batch: 123456
Lot: 123456
Exp: 1-1-11
MEDTECH

Federal law prohibits the transfer of this drug to any other person than the patient for whom prescribed.